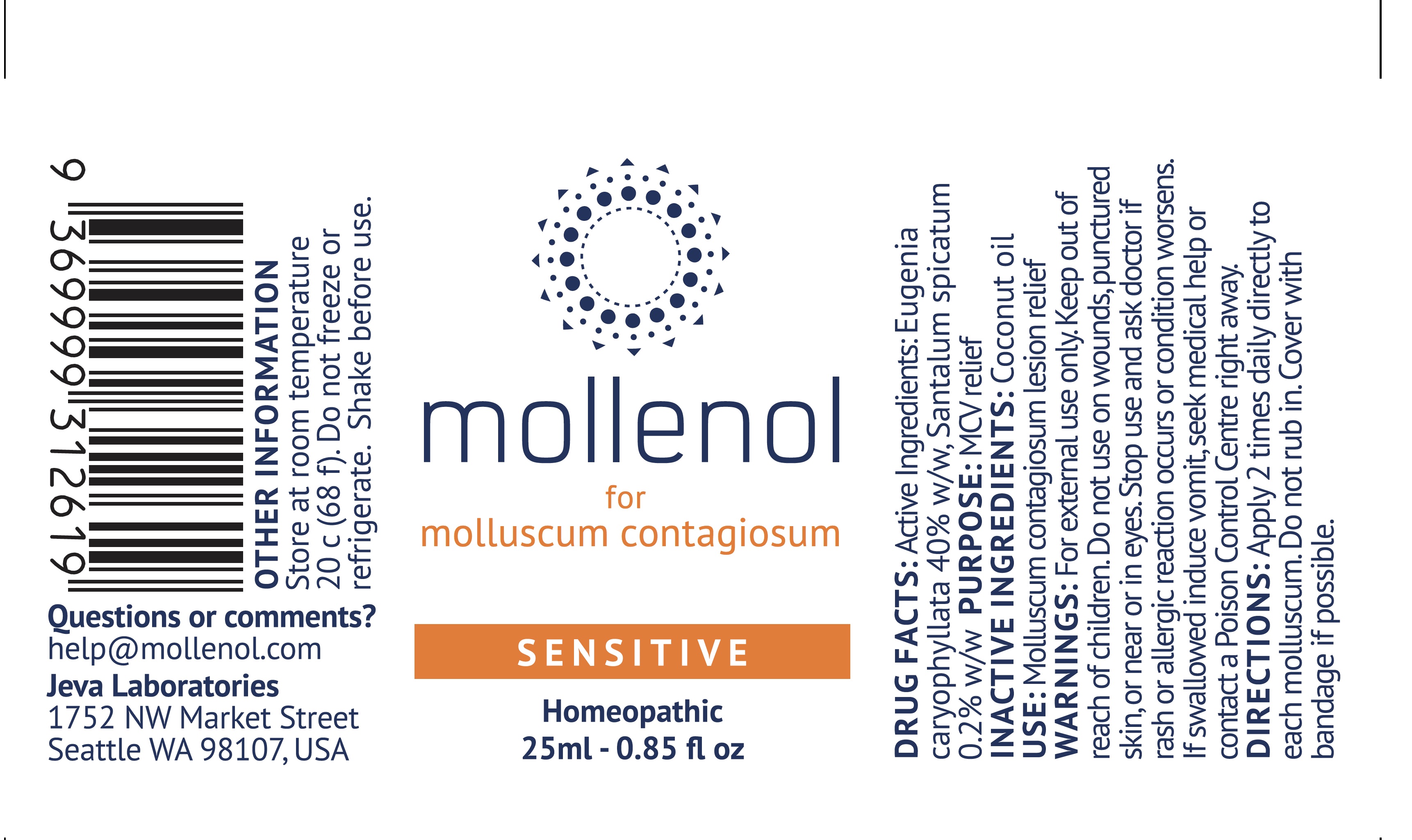 DRUG LABEL: Mollenol Sensitive
NDC: 72269-020 | Form: OINTMENT
Manufacturer: Jeva Laboratories
Category: homeopathic | Type: HUMAN OTC DRUG LABEL
Date: 20181015

ACTIVE INGREDIENTS: CLOVE 40 mg/100 mL; SANTALUM SPICATUM WHOLE 0.2 mg/100 mL
INACTIVE INGREDIENTS: COCONUT OIL

Mollenol Sensitive

ACTIVE INGREDIENT

Eugenia caryophylata 40% w/w

Santalum Spicatum 0.2% w/w

INACTIVE INGREDIENT

Coconut Oil

INDICATIONS AND USAGE

MCV relief

Molluscum contagiosum lesion relief.

PURPOSE

MCV Relief

DOSAGE AND ADMINISTRATION

Apply 2 times daily directly to each molluscum

Do not rub in.

Cover with bandage if possible.

WARNINGS

For external use only.

Keep out of reach of children.

Do not use on wounds, punctured skin or near or in eyes.

Stop use and ask doctor if rash or allergic reaction occurs or condition worsens.

If swallowed induce vomit, seek medical help, or contact a Poison Control Center right away.

Keep out of reach of children.